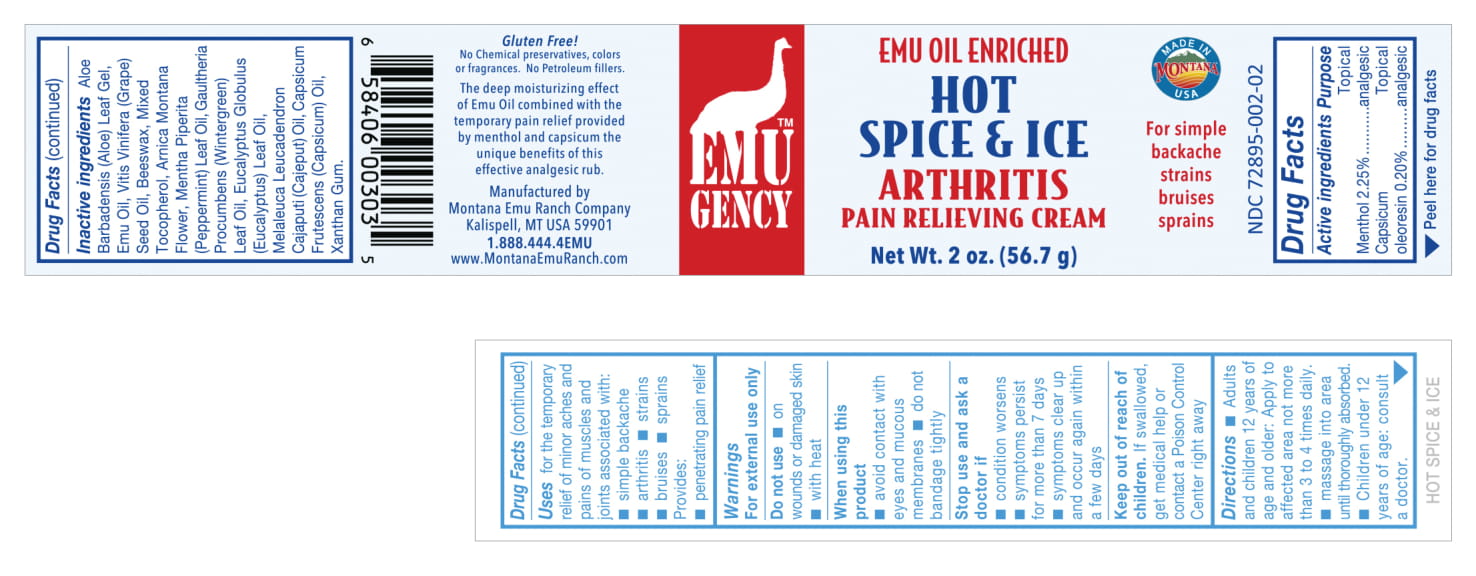 DRUG LABEL: Hot Spice and Ice
NDC: 72895-002 | Form: CREAM
Manufacturer: laiden montana emu products
Category: otc | Type: HUMAN OTC DRUG LABEL
Date: 20200101

ACTIVE INGREDIENTS: MENTHOL 1.28 g/56.7 g; CAPSICUM OLEORESIN 113 mg/56.7 g
INACTIVE INGREDIENTS: ALOE VERA LEAF; XANTHAN GUM; METHYL SALICYLATE; EUCALYPTUS GLOBULUS LEAF; MELALEUCA CAJUPUTI LEAF OIL; GRAPE SEED OIL; YELLOW WAX; ARNICA MONTANA FLOWER; PEPPERMINT OIL; TABASCO PEPPER; EMU OIL; TOCOPHEROL

Hot Spice and Ice Arthritis Pain Relieving Cream 2 oz

Active Ingredients

Menthol 2.25%

Capsicum oleoresin 0.20%

Uses

Uses for the temporary relief of minor aches and pains of muscles and joints associated with:

- simple backache
- arthritis
- strains
- bruises
- sprains

Provides:

- penetrating pain relief

Warnings

For external use only

Do not use

- on wounds or damaged skin
- with heat

When using this product

- avoid contact with eyes and mucous membranes
- do not bandage tightly

Stop use and ask a doctor if

- condition worsens
- symptoms persist for more than 7 days
- symptoms clear up and occur again within a few days

Keep out of reach of children. If swallowed, get medical help or contact a Poison Control Center right away.

Directions

- Adults and children 12 years of age and older: Apply to affected area not more than 3 to 4 times daily.
- massage into area until thoroughly absorbed
- Children under 12 years of age: consult a doctor.

Inactive Ingredients

Inactive ingredients Aloe Barbadensis (Aloe) Leaf Gel, Emu Oil, Vitis Vinifera (Grape) Seed Oil, Beeswax, Mixed Tocopherol, Arnica Montana Flower, Mentha Piperita (Peppermint) Leaf Oil, Gaultheria Procumbens (Wintergreen) Leaf Oil, Eucalyptus Globulus (Eucalyptus) Leaf Oil, Melaleuca Leucadendron Cajaputi (Cajeput) Oil, Capsicum Frutescens (Capsicum) Oil, Xanthan Gum

Purpose

Topical analgesic

Principal Display Panel

Hot Spice and Ice

Arthritis Pain Relieving Cream

Display Panel